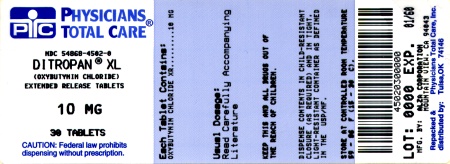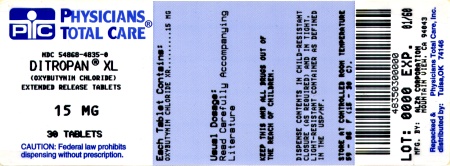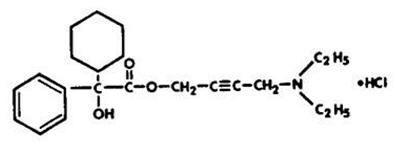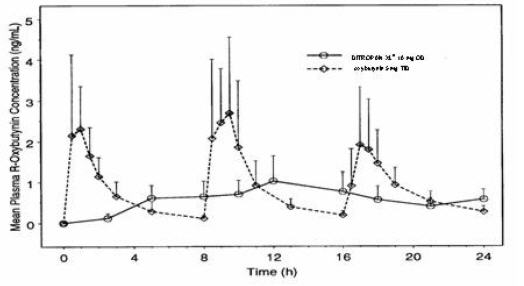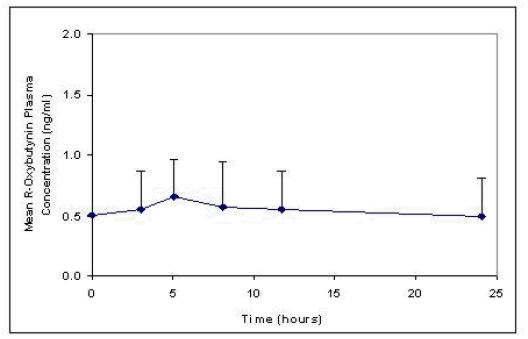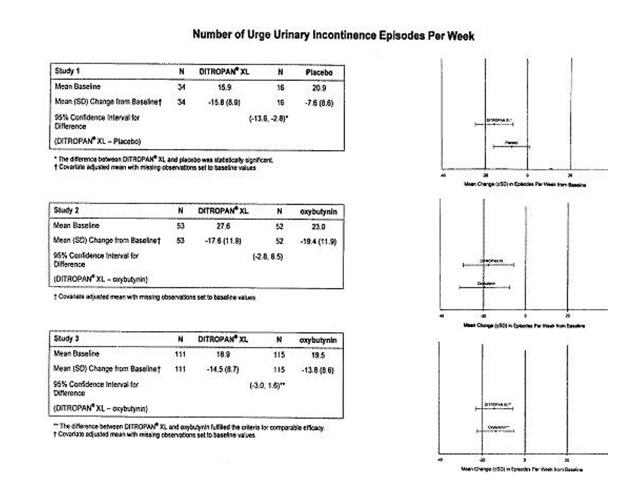 DRUG LABEL: Ditropan
NDC: 54868-4610 | Form: TABLET, EXTENDED RELEASE
Manufacturer: Physicians Total Care, Inc.
Category: prescription | Type: HUMAN PRESCRIPTION DRUG LABEL
Date: 20120216

ACTIVE INGREDIENTS: oxybutynin chloride 5 mg/1 1
INACTIVE INGREDIENTS: cellulose acetate; hypromelloses; lactose; magnesium stearate; polyethylene glycols; titanium dioxide; polysorbate 80; sodium chloride; butylated hydroxytoluene

DITROPAN XL®
(oxybutynin chloride)
Extended Release Tablets

DESCRIPTION

DITROPAN XL® (oxybutynin chloride) is an antispasmodic, anticholinergic agent. Each DITROPAN XL® Extended Release Tablet contains 5 mg, 10 mg, or 15 mg of oxybutynin chloride USP, formulated as a once-a-day controlled-release tablet for oral administration. Oxybutynin chloride is administered as a racemate of R- and S-enantiomers.

Chemically, oxybutynin chloride is d,l (racemic) 4-diethylamino-2-butynyl phenylcyclohexylglycolate hydrochloride. The empirical formula of oxybutynin chloride is C22H31NO3•HCl.

Its structural formula is:

Oxybutynin chloride is a white crystalline solid with a molecular weight of 393.9. It is readily soluble in water and acids, but relatively insoluble in alkalis.

DITROPAN XL® also contains the following inert ingredients: cellulose acetate, hypromellose, lactose, magnesium stearate, polyethylene glycol, polyethylene oxide, synthetic iron oxides, titanium dioxide, polysorbate 80, sodium chloride, and butylated hydroxytoluene.

System Components and Performance

DITROPAN XL® uses osmotic pressure to deliver oxybutynin chloride at a controlled rate over approximately 24 hours. The system, which resembles a conventional tablet in appearance, comprises an osmotically active bilayer core surrounded by a semipermeable membrane. The bilayer core is composed of a drug layer containing the drug and excipients, and a push layer containing osmotically active components. There is a precision-laser drilled orifice in the semipermeable membrane on the drug-layer side of the tablet. In an aqueous environment, such as the gastrointestinal tract, water permeates through the membrane into the tablet core, causing the drug to go into suspension and the push layer to expand. This expansion pushes the suspended drug out through the orifice. The semipermeable membrane controls the rate at which water permeates into the tablet core, which in turn controls the rate of drug delivery. The controlled rate of drug delivery into the gastrointestinal lumen is thus independent of pH or gastrointestinal motility. The function of DITROPAN XL® depends on the existence of an osmotic gradient between the contents of the bilayer core and the fluid in the gastrointestinal tract. Since the osmotic gradient remains constant, drug delivery remains essentially constant. The biologically inert components of the tablet remain intact during gastrointestinal transit and are eliminated in the feces as an insoluble shell.

CLINICAL PHARMACOLOGY

Oxybutynin chloride exerts a direct antispasmodic effect on smooth muscle and inhibits the muscarinic action of acetylcholine on smooth muscle. Oxybutynin chloride exhibits only one-fifth of the anticholinergic activity of atropine on the rabbit detrusor muscle, but four to ten times the antispasmodic activity. No blocking effects occur at skeletal neuromuscular junctions or autonomic ganglia (antinicotinic effects).

Oxybutynin chloride relaxes bladder smooth muscle. In patients with conditions characterized by involuntary bladder contractions, cystometric studies have demonstrated that oxybutynin increases bladder (vesical) capacity, diminishes the frequency of uninhibited contractions of the detrusor muscle, and delays the initial desire to void. Oxybutynin thus decreases urgency and the frequency of both incontinent episodes and voluntary urination.

Antimuscarinic activity resides predominantly in the R-isomer. A metabolite, desethyloxybutynin, has pharmacological activity similar to that of oxybutynin in in vitro studies.

Pharmacokinetics

Absorption

Following the first dose of DITROPAN XL® (oxybutynin chloride), oxybutynin plasma concentrations rise for 4 to 6 hours; thereafter steady concentrations are maintained for up to 24 hours, minimizing fluctuations between peak and trough concentrations associated with oxybutynin.

The relative bioavailabilities of R- and S-oxybutynin from DITROPAN XL® are 156% and 187%, respectively, compared with oxybutynin. The mean pharmacokinetic parameters for R- and S-oxybutynin are summarized in Table 1. The plasma concentration-time profiles for R- and S-oxybutynin are similar in shape; Figure 1 shows the profile for R-oxybutynin.

Table 1 Mean (SD) R- and S-Oxybutynin Pharmacokinetic Parameters Following a Single Dose of DITROPAN XL® 10 mg (n=43)
Parameters (units) | R-Oxybutynin |  | S-Oxybutynin
Cmax (ng/mL) | 1.0 | (0.6) | 1.8 | (1.0)
Tmax (h) | 12.7 | (5.4) | 11.8 | (5.3)
t1/2 (h) | 13.2 | (6.2) | 12.4 | (6.1)
AUC (0–48) (ng∙h/mL) | 18.4 | (10.3) | 34.2 | (16.9)
AUCinf (ng∙h/mL) | 21.3 | (12.2) | 39.5 | (21.2)

Figure 1. Mean R-oxybutynin plasma concentrations following a single dose of DITROPAN XL® 10 mg and oxybutynin 5 mg administered every 8 hours (n=23 for each treatment).

Steady state oxybutynin plasma concentrations are achieved by Day 3 of repeated DITROPAN XL® dosing, with no observed drug accumulation or change in oxybutynin and desethyloxybutynin pharmacokinetic parameters.

DITROPAN XL® steady state pharmacokinetics were studied in 19 children aged 5–15 years with detrusor overactivity associated with a neurological condition (e.g., spina bifida). The children were on DITROPAN XL® total daily dose ranging from 5 to 20 mg (0.10 to 0.77 mg/kg). Sparse sampling technique was used to obtain serum samples. When all available data are normalized to an equivalent of 5 mg per day DITROPAN XL®, the mean pharmacokinetic parameters derived for R- and S-oxybutynin and R- and S-desethyloxybutynin are summarized in Table 2. The plasma-time concentration profiles for R- and S-oxybutynin are similar in shape; Figure 2 shows the profile for R-oxybutynin when all available data are normalized to an equivalent of 5 mg per day.

Table 2 Mean ± SD R- and S-Oxybutynin and R- and S-Desethyloxybutynin Pharmacokinetic Parameters in Children Aged 5–15 Following Administration of 5 to 20 mg DITROPAN XL® Once Daily (n=19), All Available Data Normalized to an Equivalent of DITROPAN XL® 5 mg Once Daily
 | R-Oxybutynin | S-Oxybutynin | R- Desethyloxybutynin | S- Desethyloxybutynin
Cmax (ng/mL) | 0.7 ± 0.4 | 1.3 ± 0.8 | 7.8 ± 3.7 | 4.2 ± 2.3
Tmax (h) | 5.0 | 5.0 | 5.0 | 5.0
AUC(ng∙h/mL) | 12.8 ± 7.0 | 23.7 ± 14.4 | 125.1 ± 66.7 | 73.6 ± 47.7

Figure 2. Mean steady state (± SD) R-oxybutynin plasma concentrations following administration of 5 to 20 mg DITROPAN XL® once daily in children aged 5–15. Plot represents all available data normalized to an equivalent of DITROPAN XL® 5 mg once daily.

Food Effects

The rate and extent of absorption and metabolism of oxybutynin are similar under fed and fasted conditions.

Distribution

Oxybutynin is widely distributed in body tissues following systemic absorption. The volume of distribution is 193 L after intravenous administration of 5 mg oxybutynin chloride. Both enantiomers of oxybutynin are highly bound (>99%) to plasma proteins. Both enantiomers of N-desethyloxybutynin are also highly bound (>97%) to plasma proteins. The major binding protein is alpha-1 acid glycoprotein.

Metabolism

Oxybutynin is metabolized primarily by the cytochrome P450 enzyme systems, particularly CYP3A4 found mostly in the liver and gut wall. Its metabolic products include phenylcyclohexylglycolic acid, which is pharmacologically inactive, and desethyloxybutynin, which is pharmacologically active. Following DITROPAN XL® administration, plasma concentrations of R- and S-desethyloxybutynin are 73% and 92%, respectively, of concentrations observed with oxybutynin.

Excretion

Oxybutynin is extensively metabolized by the liver, with less than 0.1% of the administered dose excreted unchanged in the urine. Also, less than 0.1% of the administered dose is excreted as the metabolite desethyloxybutynin.

Dose Proportionality

Pharmacokinetic parameters of oxybutynin and desethyloxybutynin (Cmax and AUC) following administration of 5–20 mg of DITROPAN XL® are dose proportional.

Special Populations

Geriatric

The pharmacokinetics of DITROPAN XL® were similar in all patients studied (up to 78 years of age).

Pediatric

The pharmacokinetics of DITROPAN XL® were evaluated in 19 children aged 5–15 years with detrusor overactivity associated with a neurological condition (e.g., spina bifida). The pharmacokinetics of DITROPAN XL® in these pediatric patients were consistent with those reported for adults (see Tables 1 and 2, and Figures 1 and 2 above).

Gender

There are no significant differences in the pharmacokinetics of oxybutynin in healthy male and female volunteers following administration of DITROPAN XL®.

Race

Available data suggest that there are no significant differences in the pharmacokinetics of oxybutynin based on race in healthy volunteers following administration of DITROPAN XL®.

Renal Insufficiency

There is no experience with the use of DITROPAN XL® in patients with renal insufficiency.

Hepatic Insufficiency

There is no experience with the use of DITROPAN XL® in patients with hepatic insufficiency.

Drug-Drug Interactions

See PRECAUTIONS: Drug Interactions.

CLINICAL STUDIES

DITROPAN XL® (oxybutynin chloride) was evaluated for the treatment of patients with overactive bladder with symptoms of urge urinary incontinence, urgency, and frequency in three controlled studies and one open-label study. The majority of patients were Caucasian (89.0%) and female (91.9%) with a mean age of 59 years (range, 18 to 98 years). Entry criteria required that patients have urge or mixed incontinence (with a predominance of urge) as evidenced by ≥ 6 urge incontinence episodes per week and ≥ 10 micturitions per day. Study 1 was a fixed-dose escalation design, whereas the other studies used a dose-adjustment design in which each patient's final dose was adjusted to a balance between improvement of incontinence symptoms and tolerability of side effects. Controlled studies included patients known to be responsive to oxybutynin or other anticholinergic medications, and these patients were maintained on a final dose for up to 2 weeks.

The efficacy results for the three controlled trials are presented in the following tables and figures.

INDICATIONS AND USAGE

DITROPAN XL® (oxybutynin chloride) is a once-daily controlled-release tablet indicated for the treatment of overactive bladder with symptoms of urge urinary incontinence, urgency, and frequency.

DITROPAN XL® is also indicated in the treatment of pediatric patients aged 6 years and older with symptoms of detrusor overactivity associated with a neurological condition (e.g., spina bifida).

CONTRAINDICATIONS

DITROPAN XL® (oxybutynin chloride) is contraindicated in patients with urinary retention, gastric retention and other severe decreased gastrointestinal motility conditions, uncontrolled narrow-angle glaucoma and in patients who are at risk for these conditions.

DITROPAN XL® is also contraindicated in patients who have demonstrated hypersensitivity to the drug substance or other components of the product.

WARNINGS

Angioedema of the face, lips, tongue and/or larynx has been reported with oxybutynin. In some cases, angioedema occurred after the first dose. Angioedema associated with upper airway swelling may be life-threatening. If involvement of the tongue, hypopharynx, or larynx occurs, oxybutynin should be promptly discontinued and appropriate therapy and/or measures necessary to ensure a patent airway should be promptly provided.

PRECAUTIONS

Central Nervous System Effects

Oxybutynin is associated with anticholinergic central nervous system (CNS) effects (see ADVERSE REACTIONS). A variety of CNS anticholinergic effects have been reported, including hallucinations, agitation, confusion and somnolence. Patients should be monitored for signs of anticholinergic CNS effects, particularly in the first few months after beginning treatment or increasing the dose. If a patient experiences anticholinergic CNS effects, dose reduction or drug discontinuation should be considered.

DITROPAN XL® should be used with caution in patients with preexisting dementia treated with cholinesterase inhibitors due to the risk of aggravation of symptoms.

General

DITROPAN XL® (oxybutynin chloride) should be used with caution in patients with hepatic or renal impairment and in patients with myasthenia gravis due to the risk of symptom aggravation.

Urinary Retention

DITROPAN XL® should be administered with caution to patients with clinically significant bladder outflow obstruction because of the risk of urinary retention (see CONTRAINDICATIONS).

Gastrointestinal Disorders

DITROPAN XL® should be administered with caution to patients with gastrointestinal obstructive disorders because of the risk of gastric retention (see CONTRAINDICATIONS).

DITROPAN XL®, like other anticholinergic drugs, may decrease gastrointestinal motility and should be used with caution in patients with conditions such as ulcerative colitis and intestinal atony.

DITROPAN XL® should be used with caution in patients who have gastroesophageal reflux and/or who are concurrently taking drugs (such as bisphosphonates) that can cause or exacerbate esophagitis.

As with any other nondeformable material, caution should be used when administering DITROPAN XL® to patients with preexisting severe gastrointestinal narrowing (pathologic or iatrogenic). There have been rare reports of obstructive symptoms in patients with known strictures in association with the ingestion of other drugs in nondeformable controlled-release formulations.

Information for Patients

Patients should be informed that oxybutynin may produce angioedema that could result in life-threatening airway obstruction. Patients should be advised to promptly discontinue oxybutynin therapy and seek immediate medical attention if they experience edema of the tongue, edema of the laryngopharynx, or difficulty breathing.

Patients should be informed that heat prostration (fever and heat stroke due to decreased sweating) can occur when anticholinergics such as oxybutynin chloride are administered in the presence of high environmental temperature.

Because anticholinergic agents such as oxybutynin may produce drowsiness (somnolence) or blurred vision, patients should be advised to exercise caution.

Patients should be informed that alcohol may enhance the drowsiness caused by anticholinergic agents such as oxybutynin.

Patients should be informed that DITROPAN XL® should be swallowed whole with the aid of liquids. Patients should not chew, divide, or crush tablets. The medication is contained within a nonabsorbable shell designed to release the drug at a controlled rate. The tablet shell is eliminated from the body; patients should not be concerned if they occasionally notice in their stool something that looks like a tablet.

DITROPAN XL® should be taken at approximately the same time each day.

Drug Interactions

The concomitant use of oxybutynin with other anticholinergic drugs or with other agents which produce dry mouth, constipation, somnolence (drowsiness), and/or other anticholinergic-like effects may increase the frequency and/or severity of such effects.

Anticholinergic agents may potentially alter the absorption of some concomitantly administered drugs due to anticholinergic effects on gastrointestinal motility. This may be of concern for drugs with a narrow therapeutic index.

Mean oxybutynin chloride plasma concentrations were approximately 2 fold higher when DITROPAN XL® was administered with ketoconazole, a potent CYP3A4 inhibitor. Other inhibitors of the cytochrome P450 3A4 enzyme system, such as antimycotic agents (e.g., itraconazole and miconazole) or macrolide antibiotics (e.g., erythromycin and clarithromycin), may alter oxybutynin mean pharmacokinetic parameters (i.e., Cmax and AUC). The clinical relevance of such potential interactions is not known. Caution should be used when such drugs are co-administered.

Carcinogenesis, Mutagenesis, Impairment of Fertility

A 24-month study in rats at dosages of oxybutynin chloride of 20, 80, and 160 mg/kg/day showed no evidence of carcinogenicity. These doses are approximately 6, 25, and 50 times the maximum human exposure, based on surface area.

Oxybutynin chloride showed no increase of mutagenic activity when tested in Schizosaccharomyces pompholiciformis, Saccharomyces cerevisiae, and Salmonella typhimurium test systems.

Reproduction studies with oxybutynin chloride in the mouse, rat, hamster, and rabbit showed no definite evidence of impaired fertility.

Pregnancy

Teratogenic Effects

Pregnancy Category B

Reproduction studies with oxybutynin chloride in the mouse, rat, hamster, and rabbit showed no definite evidence of impaired fertility or harm to the animal fetus. The safety of DITROPAN XL® administration to women who are or who may become pregnant has not been established. Therefore, DITROPAN XL® should not be given to pregnant women unless, in the judgment of the physician, the probable clinical benefits outweigh the possible hazards.

Nursing Mothers

It is not known whether oxybutynin is excreted in human milk. Because many drugs are excreted in human milk, caution should be exercised when DITROPAN XL® is administered to a nursing woman.

Pediatric Use

The safety and efficacy of DITROPAN XL® were studied in 60 children in a 24-week, open-label trial. Patients were aged 6–15 years, all had symptoms of detrusor overactivity in association with a neurological condition (e.g., spina bifida), all used clean intermittent catheterization, and all were current users of oxybutynin chloride. Study results demonstrated that administration of DITROPAN XL® 5 to 20 mg/day was associated with an increase from baseline in mean urine volume per catheterization from 108 mL to 136 mL, an increase from baseline in mean urine volume after morning awakening from 148 mL to 189 mL, and an increase from baseline in the mean percentage of catheterizations without a leaking episode from 34% to 51%.

Urodynamic results were consistent with clinical results. Administration of DITROPAN XL® resulted in an increase from baseline in mean maximum cystometric capacity from 185 mL to 254 mL, a decrease from baseline in mean detrusor pressure at maximum cystometric capacity from 44 cm H2O to 33 cm H2O, and a reduction in the percentage of patients demonstrating uninhibited detrusor contractions (of at least 15 cm H2O) from 60% to 28%.

DITROPAN XL® is not recommended in pediatric patients who cannot swallow the tablet whole without chewing, dividing, or crushing, or in children under the age of 6 (See DOSAGE AND ADMINISTRATION).

Geriatric Use

The rate and severity of anticholinergic effects reported by patients less than 65 years old and those 65 years and older were similar (see CLINICAL PHARMACOLOGY, Pharmacokinetics, Special Populations: Geriatric).

ADVERSE REACTIONS

Adverse Events with DITROPAN XL®

The safety and efficacy of DITROPAN XL® (oxybutynin chloride) were evaluated in a total of 580 participants who received DITROPAN XL® in 4 clinical trials (429 patients) and four pharmacokinetic studies (151 healthy volunteers). The 429 patients were treated with 5–30 mg/day for up to 4.5 months. Three of the 4 clinical trials allowed dose adjustments based on efficacy and adverse events and one was a fixed-dose escalation design. Safety information is provided for 429 patients from these three controlled clinical studies and one open-label study in the first column of Table 3 below.

Adverse events from two additional fixed-dose, active-controlled, 12-week treatment duration, postmarketing studies, in which 576 patients were treated with DITROPAN XL® 10 mg/day, are also listed in Table 3 (second column). The adverse events are reported regardless of causality.

Table 3 Incidence (%) of Adverse Events Reported by ≥ 5% of Patients Using DITROPAN XL® (5–30 mg/day) and % of Corresponding Adverse Events in Two Fixed-Dose (10 mg/day) Studies
 |  | DITROPAN XL® | DITROPAN XL®
Body System | Adverse Event | 5–30 mg/day (n=429) | 10 mg/day (n=576)
General | headache | 10 | 6
 | asthenia | 7 | 3
 | pain | 7 | 4
Digestive | dry mouth | 61 | 29
 | constipation | 13 | 7
 | diarrhea | 9 | 7
 | nausea | 9 | 2
 | dyspepsia | 7 | 5
Nervous | somnolence | 12 | 2
 | dizziness | 6 | 4
Respiratory | rhinitis | 6 | 2
Special senses | blurred vision | 8 | 1
 | dry eyes | 6 | 3
Urogenital | urinary tract infection | 5 | 5

The most common adverse events reported by the 429 patients receiving 5–30 mg/day DITROPAN XL® were the expected side effects of anticholinergic agents. The incidence of dry mouth was dose-related.

The discontinuation rate for all adverse events was 6.8% in the 429 patients from the 4 studies of efficacy and safety who received 5–30 mg/day. The most frequent adverse event causing early discontinuation of study medication was nausea (1.9%), while discontinuation due to dry mouth was 1.2%.

In addition, the following adverse events were reported by ≥ 1 to < 5% of all patients who received DITROPAN XL® in the 6 adjustable and fixed-dose efficacy and safety studies. Infections and infestations: nasopharyngitis, upper respiratory tract infection, sinusitis, bronchitis, cystitis; Psychiatric disorders: insomnia, depression, nervousness, confusional state; Nervous System Disorders: dysgeusia; Cardiac disorders: palpitations; Vascular disorders: hypertension; Respiratory, thoracic and mediastinal disorders: nasal dryness, cough, pharyngolaryngeal pain, dry throat; Gastrointestinal Disorders: gastroesophageal reflux disease, abdominal pain, loose stools, flatulence, vomiting; Skin and subcutaneous tissue disorders: dry skin, pruritis; Musculoskeletal and connective tissue disorders: back pain, arthralgia, pain in extremity; Renal and urinary disorders: urinary retention, urinary hesitation, dysuria; General disorders and administration site conditions: fatigue, edema peripheral, asthenia, chest pain; Investigations: blood pressure increased.

Postmarketing Surveillance

Because postmarketing reactions are reported voluntarily from a population of uncertain size, it is not always possible to reliably estimate their frequency or establish a causal relationship to drug exposure. The following additional adverse drug reactions have been reported from worldwide postmarketing experience with DITROPAN XL®: Psychiatric Disorders: psychotic disorder, agitation, hallucinations, memory impairment; Nervous System Disorders: convulsions; Eye Disorders: glaucoma; Cardiac Disorders: arrhythmia, tachycardia, QT interval prolongation; Vascular Disorders: flushing; Skin and Subcutaneous Tissue Disorders: rash; Renal and Urinary Disorders: impotence; General Disorders and Administration Site Conditions: hypersensitivity reactions, including angioedema with airway obstruction, urticaria, and face edema; rare anaphylactic reactions requiring hospitalization for emergency treatment; Injury, poisoning and procedural complications: fall.

Additional adverse events reported with some other oxybutynin chloride formulations include: cycloplegia, mydriasis, and suppression of lactation.

OVERDOSAGE

The continuous release of oxybutynin from DITROPAN XL® (oxybutynin chloride) should be considered in the treatment of overdosage. Patients should be monitored for at least 24 hours. Treatment should be symptomatic and supportive. Activated charcoal as well as a cathartic may be administered.

Overdosage with oxybutynin chloride has been associated with anticholinergic effects including central nervous system excitation, flushing, fever, dehydration, cardiac arrhythmia, vomiting, and urinary retention.

Ingestion of 100 mg oxybutynin chloride in association with alcohol has been reported in a 13-year-old boy who experienced memory loss, and a 34-year-old woman who developed stupor, followed by disorientation and agitation on awakening, dilated pupils, dry skin, cardiac arrhythmia, and retention of urine. Both patients fully recovered with symptomatic treatment.

DOSAGE AND ADMINISTRATION

DITROPAN XL® (oxybutynin chloride) must be swallowed whole with the aid of liquids, and must not be chewed, divided, or crushed.

DITROPAN XL® may be administered with or without food.

Adults

The recommended starting dose of DITROPAN XL® is 5 or 10 mg once daily at approximately the same time each day. Dosage may be adjusted in 5-mg increments to achieve a balance of efficacy and tolerability (up to a maximum of 30 mg/day). In general, dosage adjustment may proceed at approximately weekly intervals.

Pediatric Patients Aged 6 Years of Age and Older

The recommended starting dose of DITROPAN XL® is 5 mg once daily at approximately the same time each day. Dosage may be adjusted in 5-mg increments to achieve a balance of efficacy and tolerability (up to a maximum of 20 mg/day).

HOW SUPPLIED

DITROPAN XL® (oxybutynin chloride) Extended Release Tablets are available in three dosage strengths, 10 mg (pink), and 15 mg (gray) and are imprinted with "10 XL", or "15 XL". DITROPAN XL® Extended Release Tablets are supplied in

10 mg | 10 count bottle | NDC 54868-4502-1
 | 30 count bottle | NDC 54868-4502-0
15 mg | 10 count bottle | NDC 54868-4835-1
 | 30 count bottle | NDC 54868-4835-0

Storage

Store at 25°C (77°F); excursions permitted to 15–30°C (59–86°F) [see USP Controlled Room Temperature]. Protect from moisture and humidity.

For more information call 1-888-395-1232 or visit www.DITROPANXL.com

Manufactured by:
ALZA Corporation, Vacaville, CA 95688

An ALZA OROS® Technology Product

DITROPAN XL® and OROS® are registered trademarks of ALZA Corporation.

Manufactured for:
Ortho Women's Health & Urology, Division of Ortho-McNeil-Janssen Pharmaceuticals, Inc.
Raritan, NJ 08869

Placeholder for Ortho Women's Health & Urology, Division of Ortho-McNeil-Janssen Pharmaceuticals, Inc. Logo

© Ortho-McNeil-Janssen Pharmaceuticals, Inc. 1998

10192603

Revised December 2011

Relabeling and Repackaging by:
Physicians Total Care, Inc.
Tulsa, Oklahoma 74146

PRINCIPAL DISPLAY PANEL - 10 mg bottle

DITROPAN XL®
(oxybutynin chloride)
Extended-release tablets

10 mg

Rx only

PRINCIPAL DISPLAY PANEL - 15 mg bottle

DITROPAN XL®
(oxybutynin chloride)
Extended-release tablets

15 mg

Rx only